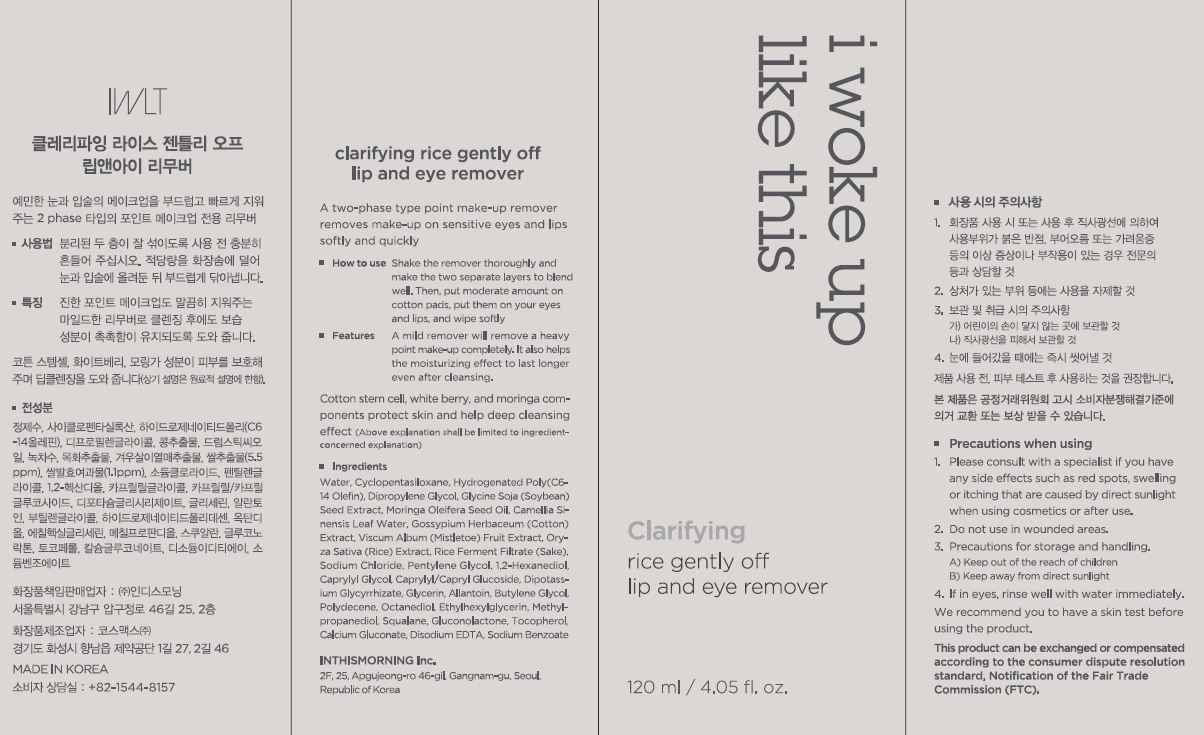 DRUG LABEL: Claritying rice gently off lip and eye remover
NDC: 71217-0066 | Form: LIQUID
Manufacturer: inthismorning co ltd
Category: otc | Type: HUMAN OTC DRUG LABEL
Date: 20230131

ACTIVE INGREDIENTS: RICE GERM 0.00055 g/100 mL
INACTIVE INGREDIENTS: WATER; GLYCERIN

Drug Facts

ACTIVE INGREDIENT

Oryza Sativa (Rice) Extract

INACTIVE INGREDIENT

Water
Cyclopentasiloxane
Hydrogenated Poly(C6-14 Olefin)
Dipropylene Glycol
Sodium Chloride
Pentylene Glycol
1,2-Hexanediol
Caprylyl Glycol
Caprylyl/Capryl Glucoside
Dipotassium Glycyrrhizate
Butylene Glycol
Glycerin
Allantoin
Disodium EDTA
Glycine Soja (Soybean) Seed Extract
Moringa Oleifera Seed Oil
Octanediol
Hydrogenated Polydecene
Camellia Sinensis Leaf Water
Ethylhexylglycerin
Rice Ferment Filtrate (Sake)
Gossypium Herbaceum (Cotton) Extract
Squalane
Viscum Album (Mistletoe) Fruit Extract
Methylpropanediol
Gluconolactone
Sodium Benzoate
Tocopherol
Calcium Gluconate

PURPOSE

removes make-up on sensitive eyes and lips softly and quickly

keep out or reach of the children

INDICATIONS AND USAGE

shake the remover thoroughly and make the two separate layers to blend well, then put moderate amount on cotton pads, put them on your eyes and lips , and wipe softly

WARNINGS

This product is for exeternal use only. Do not use for internal use
Storage and handling precautions
If possible, avoid direct sunlight and store in cool and area of low humidity in order to maintain the quality of the product and avoid misuse
Avoid placing the product near fire and store out in reach of children

- consult a physician in case of abnormal symptoms, such as red spots, swelling or itching, or side effects in the areas of application due to direct light during or after using the product

- do not use on wounded area

DOSAGE AND ADMINISTRATION

for external use only